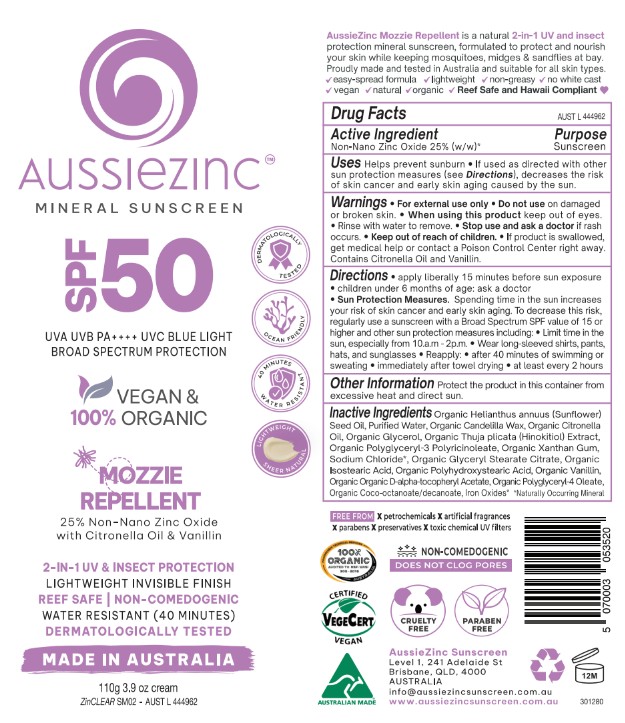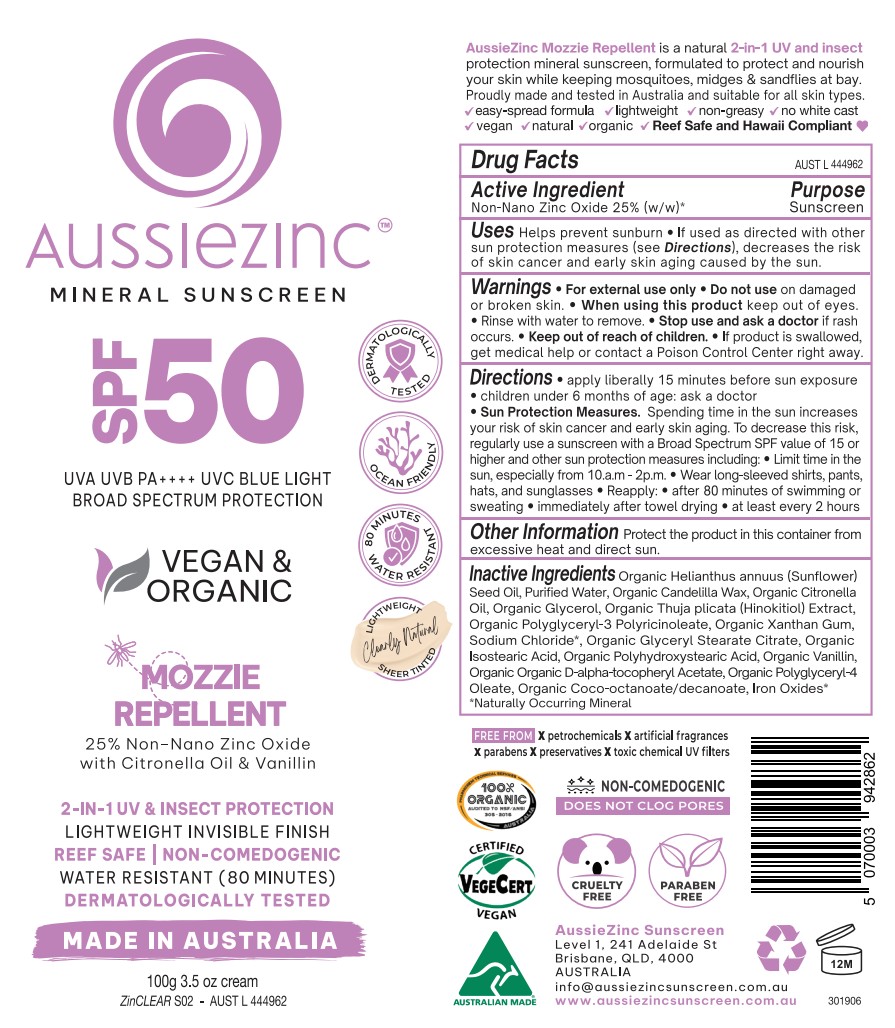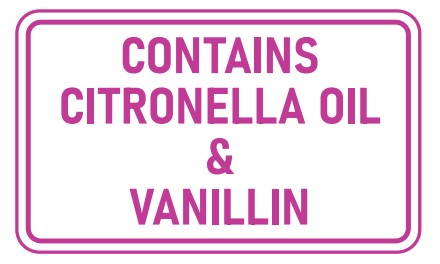 DRUG LABEL: AussieZinc Mineral Sunscreen Vegan and Organic Mozzie Repellant
NDC: 83252-101 | Form: CREAM
Manufacturer: VEGANIC SKN LIMITED
Category: otc | Type: HUMAN OTC DRUG LABEL
Date: 20251120

ACTIVE INGREDIENTS: ZINC OXIDE 25 kg/100 kg
INACTIVE INGREDIENTS: HELIANTHUS ANNUUS (SUNFLOWER) SEED OIL; TOCOPHEROL; WATER; POLYHYDROXYSTEARIC ACID (2300 MW); ISOSTEARIC ACID; CANDELILLA WAX; SODIUM CHLORIDE; GLYCERIN; POLYGLYCERYL-3 RICINOLEATE; XANTHAN GUM; FERRIC OXIDE RED; SODIUM HINOKITIOL; FERRIC OXIDE YELLOW; FERROSOFERRIC OXIDE; VANILLIN; COCO-CAPRYLATE/CAPRATE; POLYGLYCERYL-4 OLEATE; GLYCERYL STEARATE CITRATE; CITRONELLA OIL; COCONUT ALKANES

AussieZinc Mineral Sunscreen Vegan and Organic Mozzie Repellant

WARNINGS

For external use only.

Do not use on damaged r broken skin.

When using this product keep out of eyes. Rinse with water to remove.
Stop use and ask a doctor if rash occurs.

Keep out of reach of children.

If product is swallowed, get medical help or contact a Poison Control Center right away.

Keep out of reach of children.

INACTIVE INGREDIENT

See ingredients on label